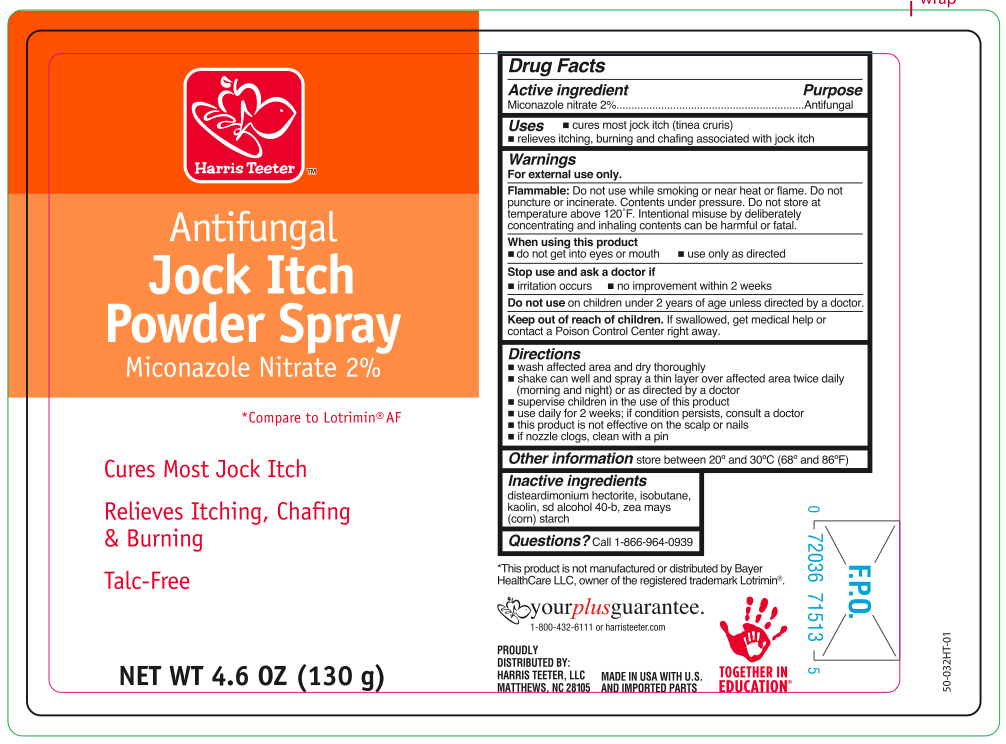 DRUG LABEL: Miconazole Nitrate
NDC: 69256-038 | Form: AEROSOL, SPRAY
Manufacturer: Harris Teeter, LLC
Category: otc | Type: HUMAN OTC DRUG LABEL
Date: 20251030

ACTIVE INGREDIENTS: MICONAZOLE NITRATE 1.3 g/130 g
INACTIVE INGREDIENTS: ISOBUTANE; KAOLIN; ALCOHOL; ZEA MAYS SUBSP. MAYS WHOLE; DISTEARDIMONIUM HECTORITE

Harris Teeter Miconazole Antifungal Jock Itch Powder Spray Talc-Free

Active ingredient

Miconazole nitrate 2%

Purpose

Antifungal

Uses

- cures most jock itch (tinea cruris)
- relieves symptoms of jock itch including itching, burning and chafing associated with jock itch

Warnings

For external use only.

Flammable:

Do not use while smoking or near heat or flame. Do not puncture or incinerate. Contents under pressure. Do not store at temperature above 120ºF.

When using this product

- do not get into eyes or mouth
- use only as directed. Intentional misuse by deliberately concentrating and inhaling contents cans be harmful or fatal.

Stop use and ask a doctor if

- irritation occurs
- no improvement within 2 weeks for jock itch

Keep out of reach of children.

If swallowed, get medical help or contact a Poison Control Center right away. Do not use on children under 2 years of age. Do not use for diaper rash. Do not use on children under 2 years of age unless directed by a doctor.

Directions

- wash affected area and dry thoroughly
- shake can well and spray a thin layer over affected area twice daily (morning and night)
- supervise children in the use of this product
- use daily for 2 weeks. If conditions persist, consult a doctor
- this product is not effective on scalp or nails
- in case of clogging, clear nozzle under running water

Inactive ingredient

Disteardimonium Hectorite, Isobutane, Kaolin, SD Alcohol 40-B, Zea Mays (Corn) Starch

Questions?

Call 1-866-964-0939

Principal Display Panel

Harris Teeter

Antifungal

Jock Itch

Powder Spray

MICONAZOLE NITRATE 2%

Cures Most Jock Itch

Relieves Itching, Chafing & Burning

Talc-Free

NET WT 4.6 OZ (130 g)